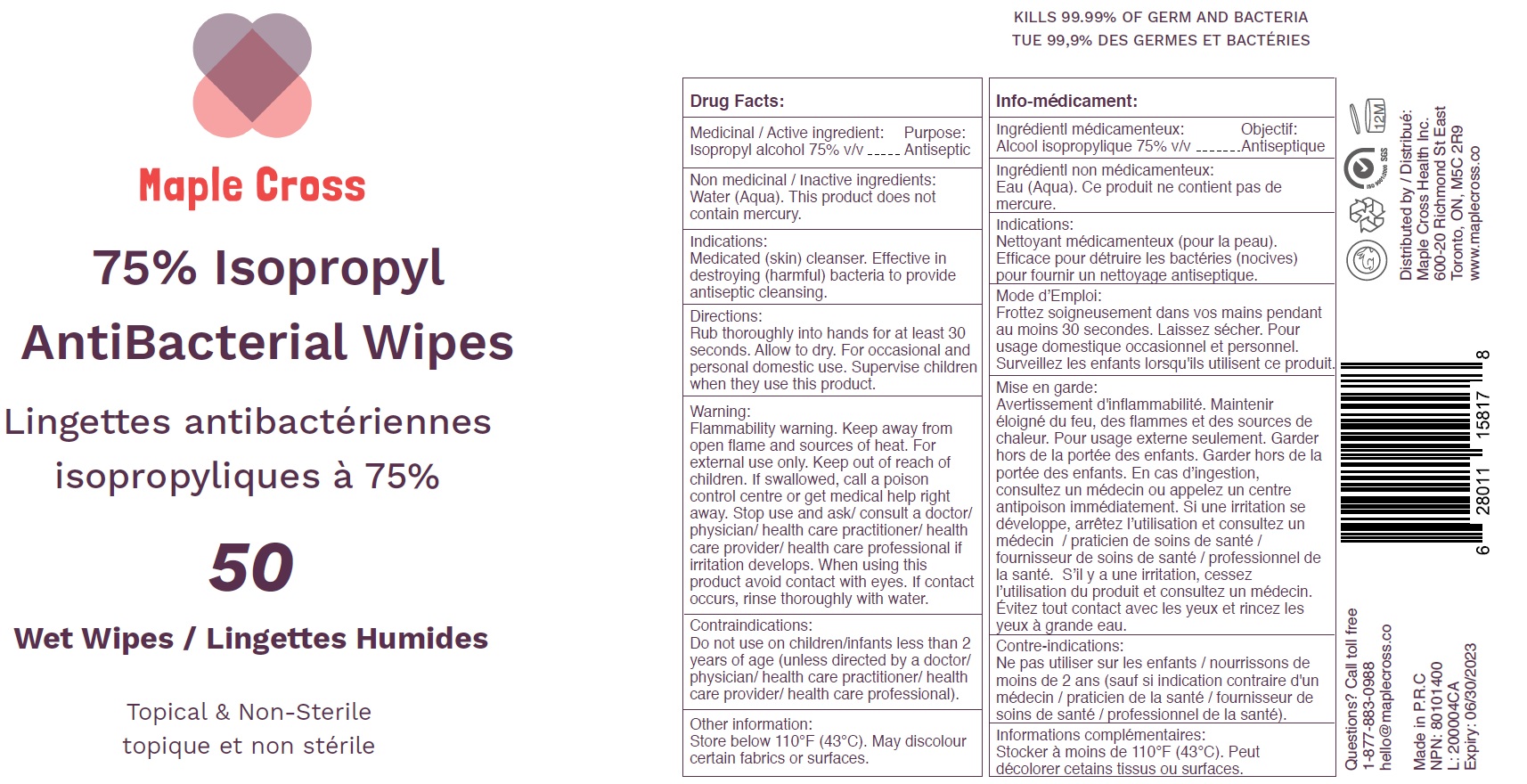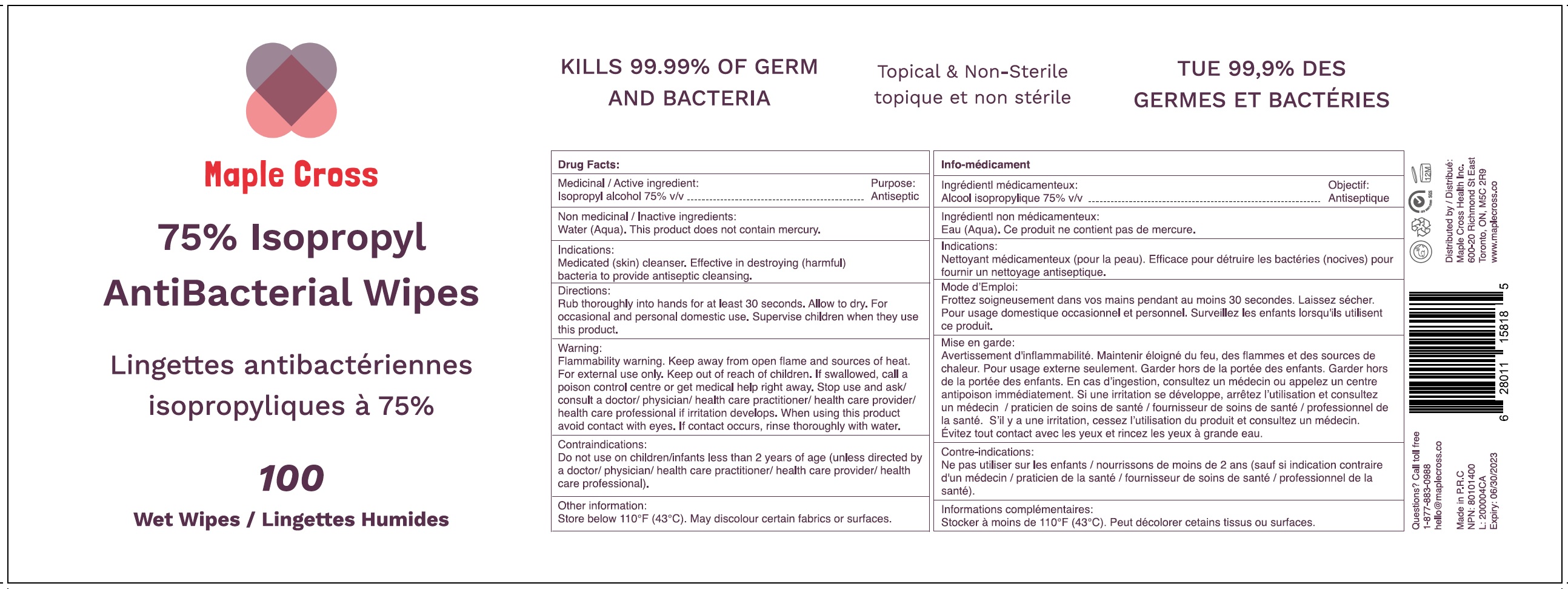 DRUG LABEL: Maple Cross 75 Isopropyl Antibacterial
NDC: 77216-003 | Form: CLOTH
Manufacturer: Maple Cross Health Inc.
Category: otc | Type: HUMAN OTC DRUG LABEL
Date: 20200707

ACTIVE INGREDIENTS: ISOPROPYL ALCOHOL 0.75 mL/1 mL
INACTIVE INGREDIENTS: WATER

Maple Cross 75% Isopropyl Antibacterial

Medicinal / Active ingredient:

Isopropyl alcohol 75% v/v

Purpose:

Antiseptic

Non medicinal / Inactive ingredients:

Water (Aqua). This product does not contain mercury.

Indications:

Medicated (skin) cleanser. Effective in destroying (harmful) bacteria to provide antiseptic cleansing.

Directions:

Rub thoroughly into hands for at least 30 seconds. Allow to dry. For occasional and personal domestic use. Supervise children when they use this product.

Warning:

Flammability warning. Keep away from open flame and sources of heat. For external use only.

Keep out of reach of children.

If swallowed, call a poison control centre or get medical help right away.

Stop use and ask/ consult a doctor

physician/ health care practitioner/ health care provider/ health care professional if irritation develops.

When using this product

avoid contact with eyes. If contact occurs, rinse thoroughly with water.

Contraindications:

Do not use on children/infants less than 2 years of age (unless directed by a doctor/ physician/ health care practitioner/ health care provider/ health care professional).

Other information:

Store below 110°F (43°C). May discolour certain fabrics or surfaces.